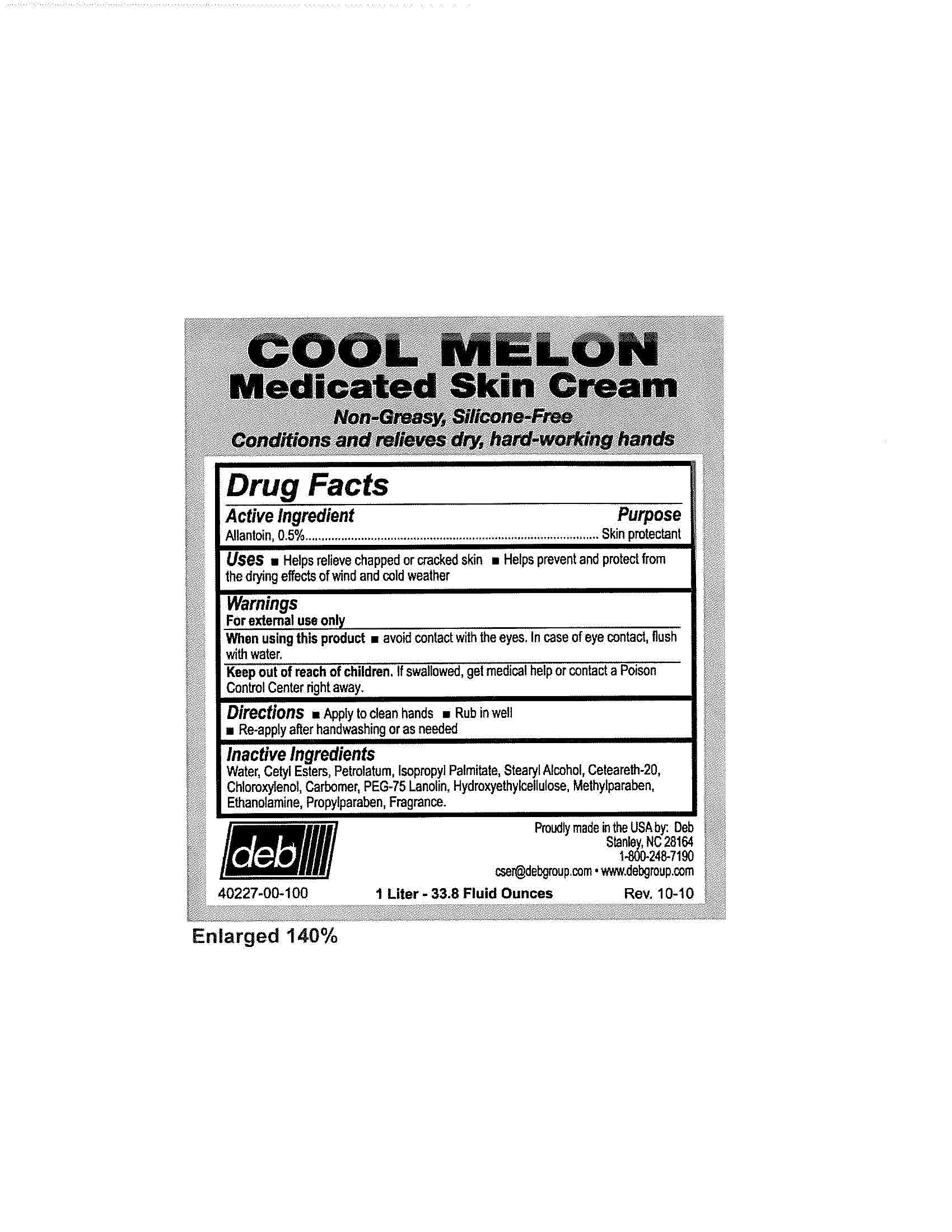 DRUG LABEL: Cool Melon
NDC: 11084-042 | Form: CREAM
Manufacturer: Deb USA, Inc.
Category: otc | Type: HUMAN OTC DRUG LABEL
Date: 20101006

ACTIVE INGREDIENTS: ALLANTOIN 0.5 mL/100 mL
INACTIVE INGREDIENTS: WATER; CETYL ESTERS WAX; PETROLATUM; ISOPROPYL PALMITATE; CHLOROXYLENOL; CARBOMER 934; HYDROXYETHYL CELLULOSE (4000 CPS AT 1%); METHYLPARABEN; ETHANOLAMINE; PROPYLPARABEN; STEARYL ALCOHOL; POLYOXYL 20 CETOSTEARYL ETHER

Drug Facts

Active Ingredient

Allantoin, 0.5%

Purpose

Skin protectant

Uses

Helps relieve chapped or cracked skin

Helps prevent and protect from the drying effects of wind and cold weather

Warnings

For external use only

When using this product avoid contact with the eyes.

In case of eye contact, flush with water.

Keep out of reach of children.

If swallowed, get medical help or contact a Poison Control Center right away.

Directions

Apply to clean hands

Rub in well

Re-apply after handwashing or as needed

Inactive Ingredients

Water, Cetyl Esters, Petrolatum, Isoproply Palmitate, Stearyl Alcohol, Ceteareth-20, Chloroxylenol, Carbomer, PEG-75 Lanolin, Hydroxyethylcellulose, Methylparaben, Ethanolamine, Propylparaben, Fragrance.

PACKAGE LABEL

Cool Melon

Medicated Skin Cream

Non-Greasy, Silicone-Free

Conditions and relieves dry, hard-working hands

deb

Proudly made in the USA by Deb

40227-00-100

1 Liter - 33.8 Fluid Ounces